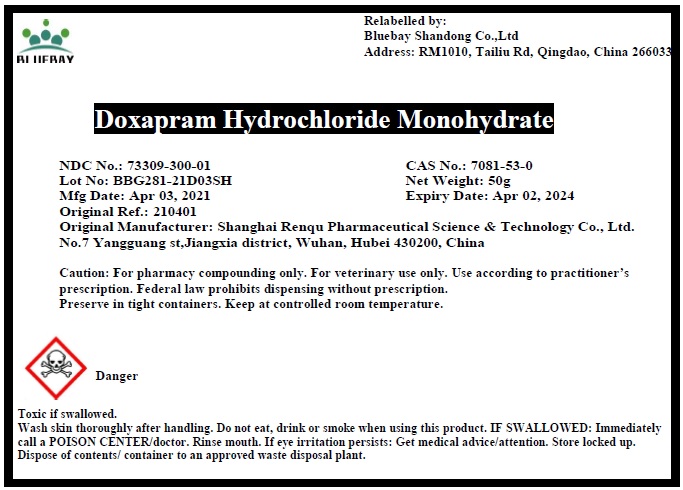 DRUG LABEL: Doxapram Hydrochloride Monohydrate
NDC: 73309-300 | Form: POWDER
Manufacturer: BLUEBAY SHANDONG CO.,LTD
Category: other | Type: BULK INGREDIENT
Date: 20210601

ACTIVE INGREDIENTS: DOXAPRAM HYDROCHLORIDE 1 g/1 g

Doxapram Hydrochloride Monohydrate